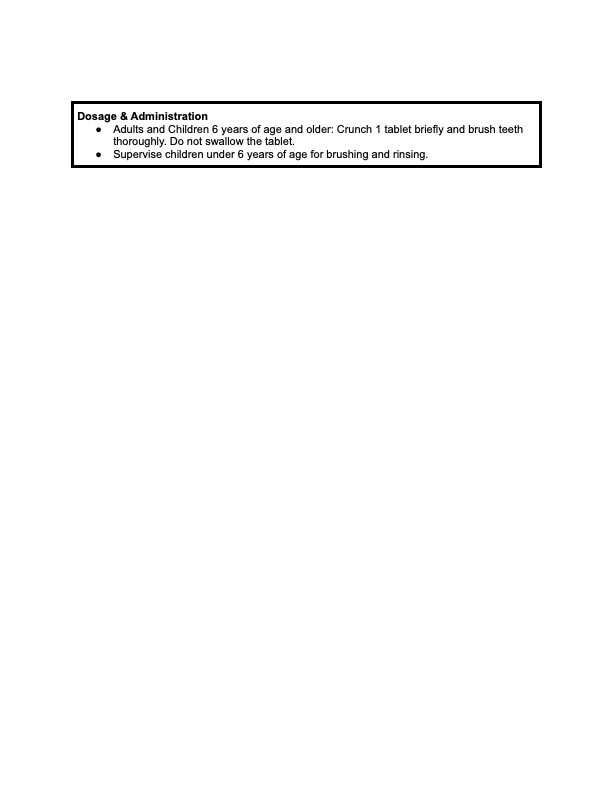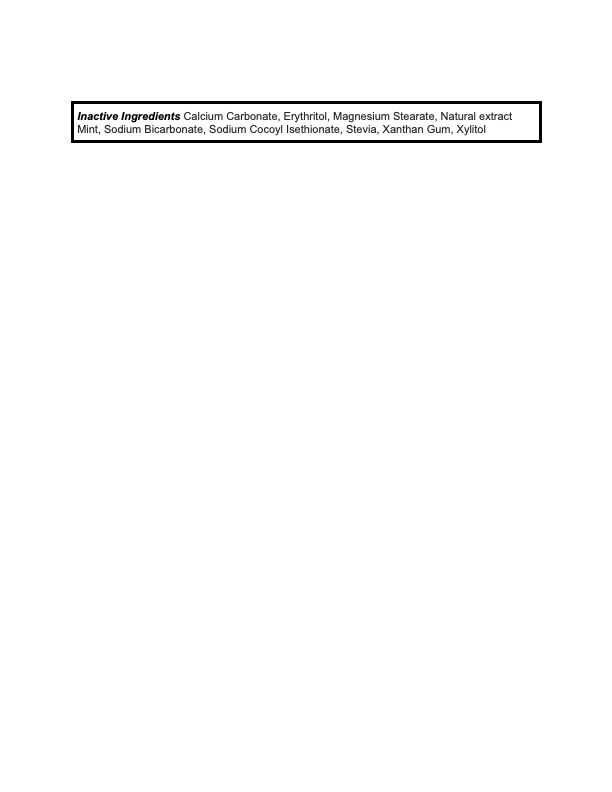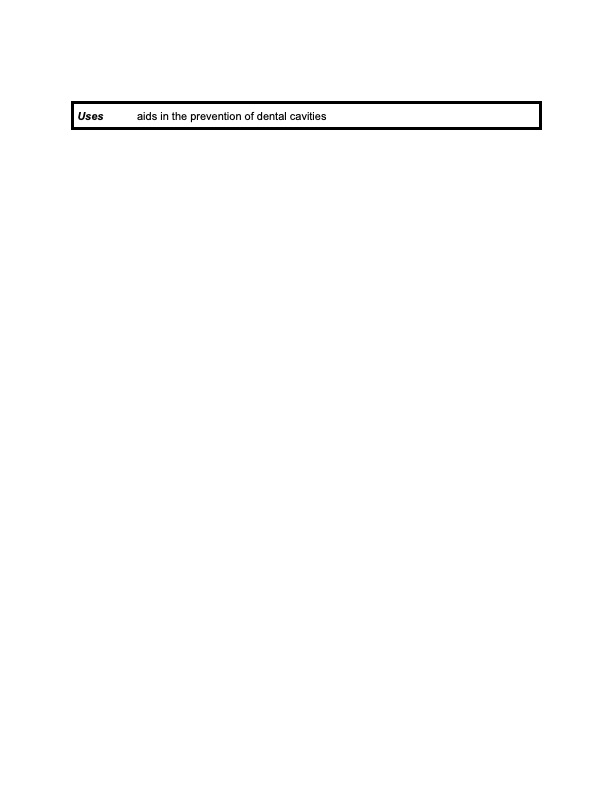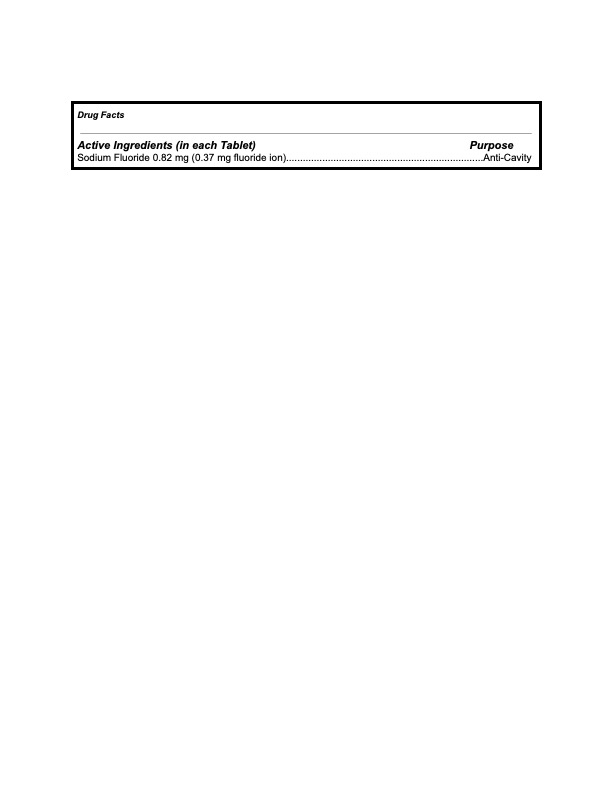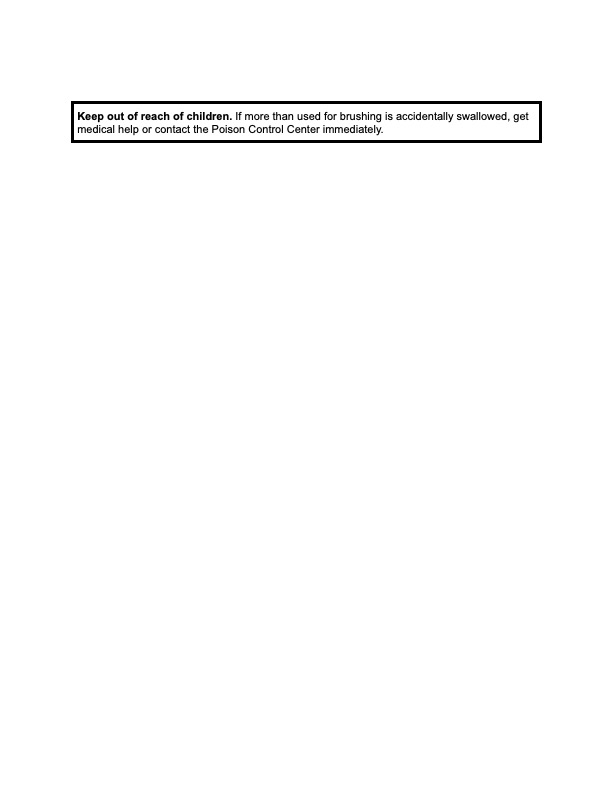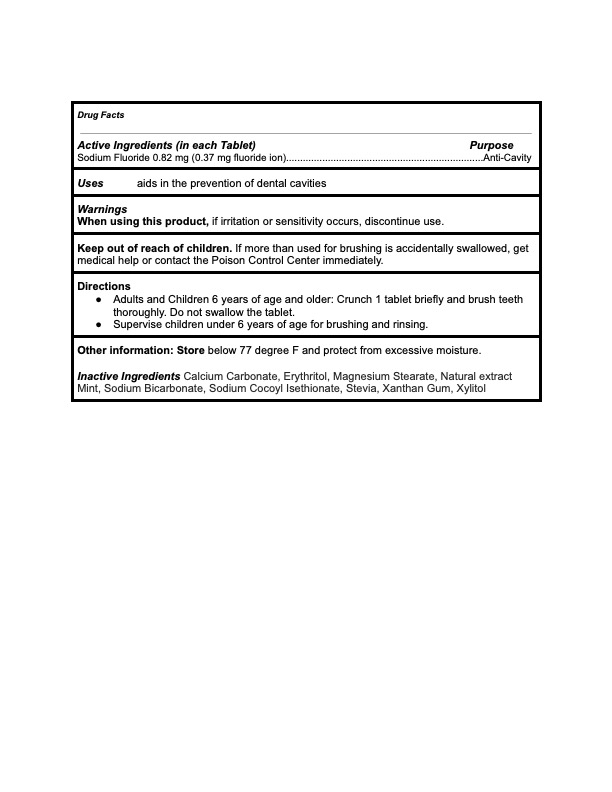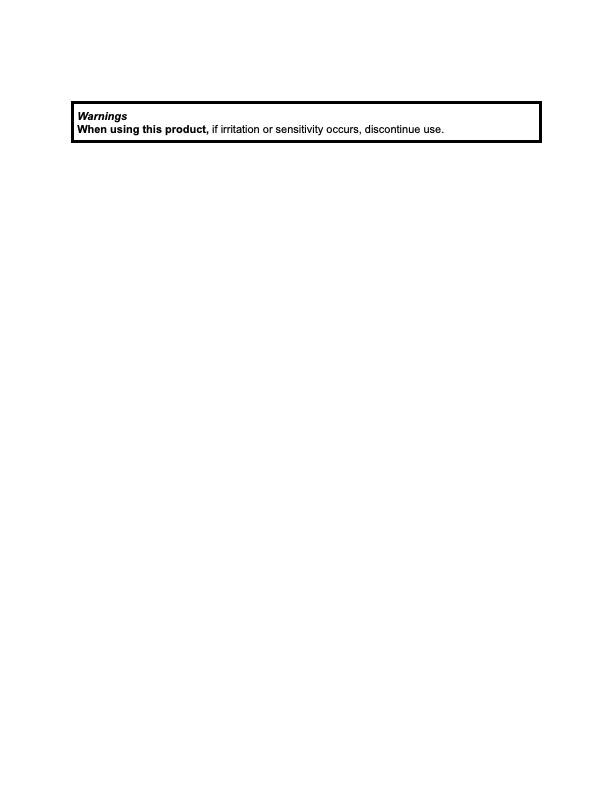 DRUG LABEL: KAYLAAN
NDC: 82091-116 | Form: TABLET, CHEWABLE
Manufacturer: Kaylaan LLC
Category: otc | Type: HUMAN OTC DRUG LABEL
Date: 20250109

ACTIVE INGREDIENTS: SODIUM FLUORIDE 0.37 mg/440 mg
INACTIVE INGREDIENTS: ERYTHRITOL; XYLITOL; SODIUM COCOYL ISETHIONATE; STEVIA LEAF; CALCIUM CARBONATE; XANTHAN GUM; WATERMELON; SODIUM BICARBONATE; MAGNESIUM STEARATE

Kaylaan Watermelon Toothpaste Tablet Refill